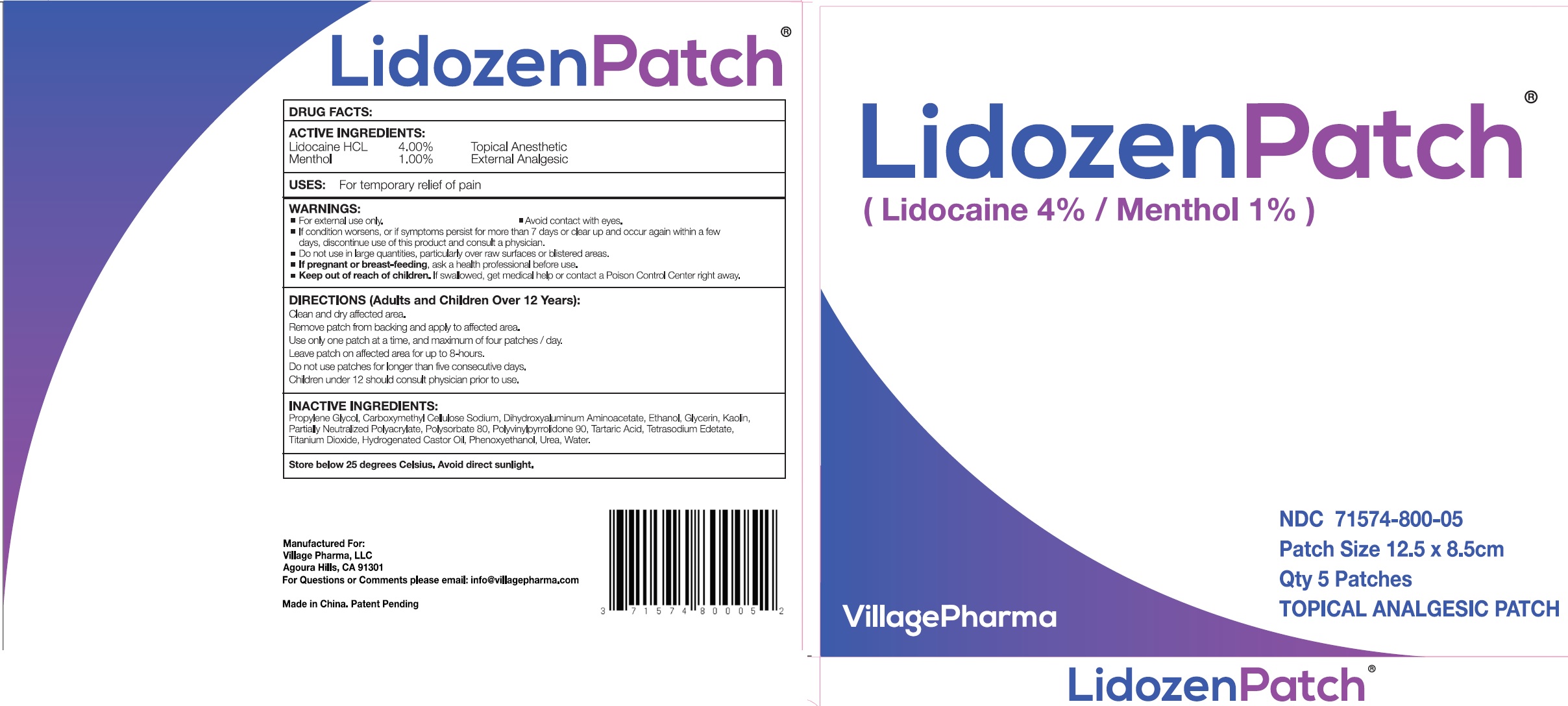 DRUG LABEL: Lidozen
NDC: 71574-800 | Form: PATCH
Manufacturer: Village Pharma LLC
Category: otc | Type: HUMAN OTC DRUG LABEL
Date: 20231129

ACTIVE INGREDIENTS: LIDOCAINE HYDROCHLORIDE 40 mg/1 g; MENTHOL 10 mg/1 g
INACTIVE INGREDIENTS: PROPYLENE GLYCOL; CARBOXYMETHYLCELLULOSE SODIUM, UNSPECIFIED FORM; DIHYDROXYALUMINUM AMINOACETATE; ALCOHOL; GLYCERIN; KAOLIN; POLYSORBATE 80; TARTARIC ACID; EDETATE SODIUM; TITANIUM DIOXIDE; HYDROGENATED CASTOR OIL; PHENOXYETHANOL; UREA; WATER

Lidozen Patch

ACTIVE INGREDIENTS:

Lidocaine HCL 4.00%

Menthol 1.00%

PURPOSE

Toplcal Anesthetic

External Analgesic

USES:

For temporary relief of pain

WARNINGS:

- For external use only.
- Avoid contact with eyes.
- If condition worsens, or if symptoms persist for more than 7 days or clear up and occur again within a few days, discontinue use of this product and consult a physician.

Do not use

in large quantities, particularly over raw surfaces or blistered areas.

If pregnant or breast-feeding,

ask a health professional before use.

Keep out of reach of children.

If swallowed, get medical help or contact a Poison Control Center right away.

DIRECTIONS (Adults and Children Over 12 Years):

Clean and dry affected area.

Remove patch from backing and apply to affected area.

Use only one patch at a time, and maximum of four patches / day.

Leave patch on affected area for up to 8 hours.

Do not use patches for longer than five consective days.

Children under 12 should consult physician prior to use.

INACTIVE INGREDIENTS:

Propylene Glycol, Carboxymethyl Cellulose Sodium, Dihydroxyaluminum Aminoacetate, Ethanol, Glycerin, Kaolin, Partially Neutralized Polyacrylate, Polysorbate 80, Polyvinylpyrrolidone 90, Tartaric Acid, Tetrasodium Edetate, Titanium Dioxide, Hydrogenated Castor Oil, Phenoxyethanol, Urea, Water.

Store below 25 degrees Celsius. Avoid directed sunlight.